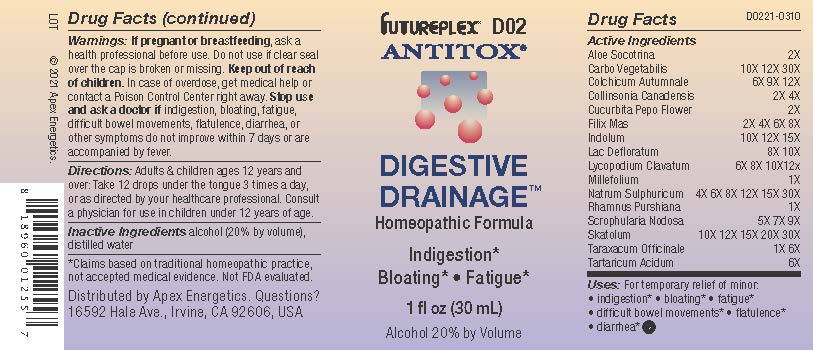 DRUG LABEL: D02
NDC: 63479-0402 | Form: SOLUTION/ DROPS
Manufacturer: Apex Energetics Inc.
Category: homeopathic | Type: HUMAN OTC DRUG LABEL
Date: 20240108

ACTIVE INGREDIENTS: FRANGULA PURSHIANA BARK 1 [hp_X]/1 mL; SCROPHULARIA NODOSA 9 [hp_X]/1 mL; ALOE 2 [hp_X]/1 mL; ACTIVATED CHARCOAL 30 [hp_X]/1 mL; COLLINSONIA CANADENSIS ROOT 4 [hp_X]/1 mL; DRYOPTERIS FILIX-MAS ROOT 8 [hp_X]/1 mL; SKIM MILK 10 [hp_X]/1 mL; TARTARIC ACID 6 [hp_X]/1 mL; SKATOLE 30 [hp_X]/1 mL; COLCHICUM AUTUMNALE BULB 12 [hp_X]/1 mL; CUCURBITA PEPO FLOWER 2 [hp_X]/1 mL; INDOLE 15 [hp_X]/1 mL; TARAXACUM OFFICINALE 6 [hp_X]/1 mL; LYCOPODIUM CLAVATUM SPORE 12 [hp_X]/1 mL; ACHILLEA MILLEFOLIUM 1 [hp_X]/1 mL; SODIUM SULFATE 30 [hp_X]/1 mL
INACTIVE INGREDIENTS: ALCOHOL; WATER

D02

Active Ingredients
ALOE SOCOTRINA | 2X
CARBO VEGETABILIS | 10X 12X 30X
COLCHICUM AUTUMNALE | 6X 9X 12X
COLLINSONIA CANADENSIS | 2X 4X
CUCURBITA PEPO FLOWER | 2X
FILIX MAS | 2X 4X 6X 8X
INDOLUM | 10X 12X 15X
LAC DEFLORATUM | 8X 10X
LYCOPODIUM CLAVATUM | 6X 8X 10X 12X
MILLEFOLIUM | 1X
NATRUM SULPHURICUM | 4X 6X 8X 12X 15X 30X
RHAMNUS PURSHIANA | 1X
SCROPHULARIA NODOSA | 5X 7X 9X
SKATOLUM | 10X 12X 15X 20X 30X
TARAXACUM OFFICINALE | 1X 6X
TARTARICUM ACIDUM | 6X

INDICATIONS AND USAGE

.

Uses:

Uses: For temporary relief of minor:

indigestion*

bloating*

fatigue*

difficult bowel movements*

flatulence*

diarrhea*

*Claims based on traditional homeopathic practice, not accepted medical evidence. Not FDA evaluated.

Warnings:

PREGNANCY OR BREAST FEEDING

If pregnant or breastfeeding, ask a health professional before use.

Do not use if clear seal over the cap is broken or missing.

Keep out of reach of children. In case of overdose, get medical help or contact a Poison Control Center right away.

Stop use and ask a doctor if indigestion, bloating, fatigue, difficult bowel movements, flatulence, diarrhea, or other symptoms do not improve within 7 days or are accompanied by fever.

Directions:

Adults & children ages 12 years and over: Take 12 drops under the tongue 3 times a day, or as directed by your healthcare professional. Consult a physician for use in children under 12 years of age.

Inactive Ingredients

alcohol (20% by volume), distilled water

Distributed by Apex Energetics. Questions?

16592 Hale Ave., Irvine, CA 92606, USA

PACKAGE LABEL

FUTUREPLEX® D02

ANTITOX®

DIGESTIVE DRAINAGE™

Homeopathic Formula

Indigestion*

Bloating*

Fatigue*

1 fl oz (30 mL)

Alcohol 20% by Volume